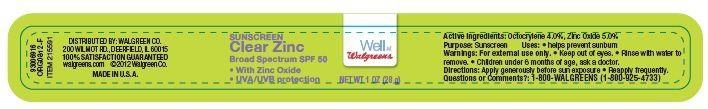 DRUG LABEL: Walgreens SUNSCREEN
NDC: 0363-4014 | Form: LOTION
Manufacturer: WALGREEN CO.
Category: otc | Type: HUMAN OTC DRUG LABEL
Date: 20130807

ACTIVE INGREDIENTS: OCTOCRYLENE 4 g/100 g; ZINC OXIDE 5 g/100 g
INACTIVE INGREDIENTS: WATER; ETHYLHEXYL STEARATE; DIISOPROPYL ADIPATE; POLYGLYCERYL-4 ISOSTEARATE; HEXYL LAURATE; YELLOW WAX; ISOHEXADECANE; SODIUM CHLORIDE; HYDROGENATED CASTOR OIL; SILICON DIOXIDE; TRIETHOXYCAPRYLYLSILANE; DIMETHICONE; TOCOPHEROL; EDETATE DISODIUM; ALOE VERA LEAF; SODIUM ASCORBYL PHOSPHATE; PHENOXYETHANOL; METHYLPARABEN; PROPYLPARABEN

Drug Facts

Active ingredients

Octocrylene 4.0%

Zinc Oxide 5.0%

Purpose

Sunscreen

Uses

- helps prevent sunburn

Warnings

For external use only.

When using this product

Keep out of eyes. Rinse with water to remove.

STOP USE

Children under 6 months of age, ask a doctor.

Questions or comments?:

1-800 WALGREENS (1-800-925-4733)

Directions

- Apply generously before sun exposure
- Reapply frequently

Inactive ingredients

Water, Ethylhexyl Stearate, Diisopropyl Adipate, Cetyl Dimethicone, Polyglyceryl-4 Isostearate, Cetyl PEG/PPG-10/1 Dimethicone, Hexyl Laurate, Beeswax, Isohexadecane, Sodium Chloride, Hydrogenated Castor Oil, Silica, Triethoxycaprylylsilane, Dimethicone,Tocopherol, Disodium EDTA, Aloe Barbadensis Leaf Juice Powder, Sodium Ascorbyl Phosphate, Phenoxyethanol, Methylparaben, Propylparaben.

Principal Display Panel

Well at

Walgreen

SUNSCREEN

Clear Zinc

Broad Spectrum SPF 50

With Zinc Oxide

UVA/UVB Protection

NET WT 1 OZ (28 g)